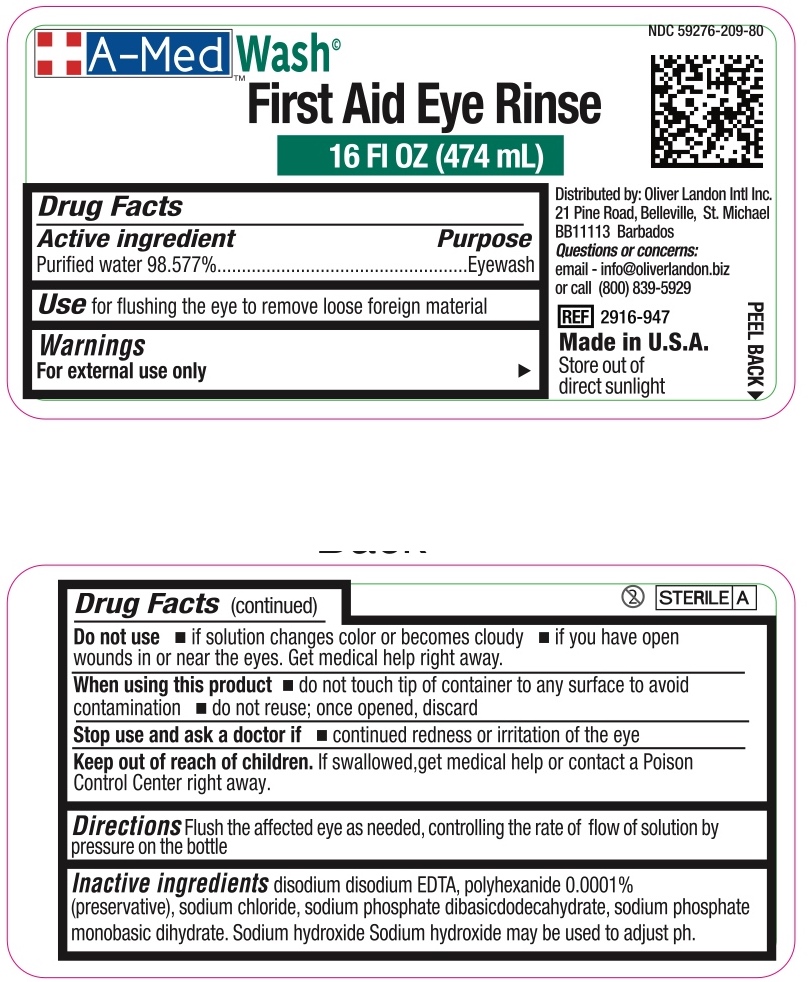 DRUG LABEL: A-Med brand First Aid Eye and Skin-Rinse
NDC: 59276-209 | Form: SOLUTION
Manufacturer: Oliver Landon Intl Inc.
Category: otc | Type: HUMAN OTC DRUG LABEL
Date: 20211205

ACTIVE INGREDIENTS: WATER 98.577 mL/100 mL
INACTIVE INGREDIENTS: POLIHEXANIDE; EDETATE DISODIUM; SODIUM HYDROXIDE; SODIUM PHOSPHATE, DIBASIC, DODECAHYDRATE; SODIUM PHOSPHATE, MONOBASIC, DIHYDRATE; SODIUM CHLORIDE

A-Med Wash First Aid Eye Rinse

Drug Facts

Active ingredient

Purified water USP 98.577% w/v

Purpose

Eyewash

INDICATIONS AND USAGE

Use for flushing the eye to remove loose foreign material.

Warnings

For external use only

Do not use

- if solution changes color or becomes cloudy
- if you have open wounds in or near the eyes. Get medical help right away.

When using this product

- do not touch tip of container to any surface to avoid contamination
- do not reuse; once opened, discard

Stop use and ask a doctor if

- continued redness or irritation of the eye

Keep out of reach of children. If swallowed, get medical help or contact a Poison Control Center right away.

DOSAGE AND ADMINISTRATION

Directions Flush the affected eye as needed, controlling the rate of flow of solution by pressure on the bottle.

INACTIVE INGREDIENT

Inactive ingredients disodium disodium EDTA, polyhexanide 0.0001% (preservative), sodium chloride, sodium phosphate dibasic dodecahydrate, sodium phosphate, monobasic dihydrate. Sodium hydroxide may be used to adjust pH.

Distributed by: Oliver Landon Intl Inc.

21 Pine Road, Belleville, St. Michael

BB 11113 Barbados

Questions or concerns:

email - info@oliverlandon.biz or call (800) 839-5929

Made in U.S.A.

Store out of direct sunlight.

PACKAGE LABEL

A-Med Wash

NDC 59276-209-80

First Aid Eye Rinse

16 FL OZ (474 mL)